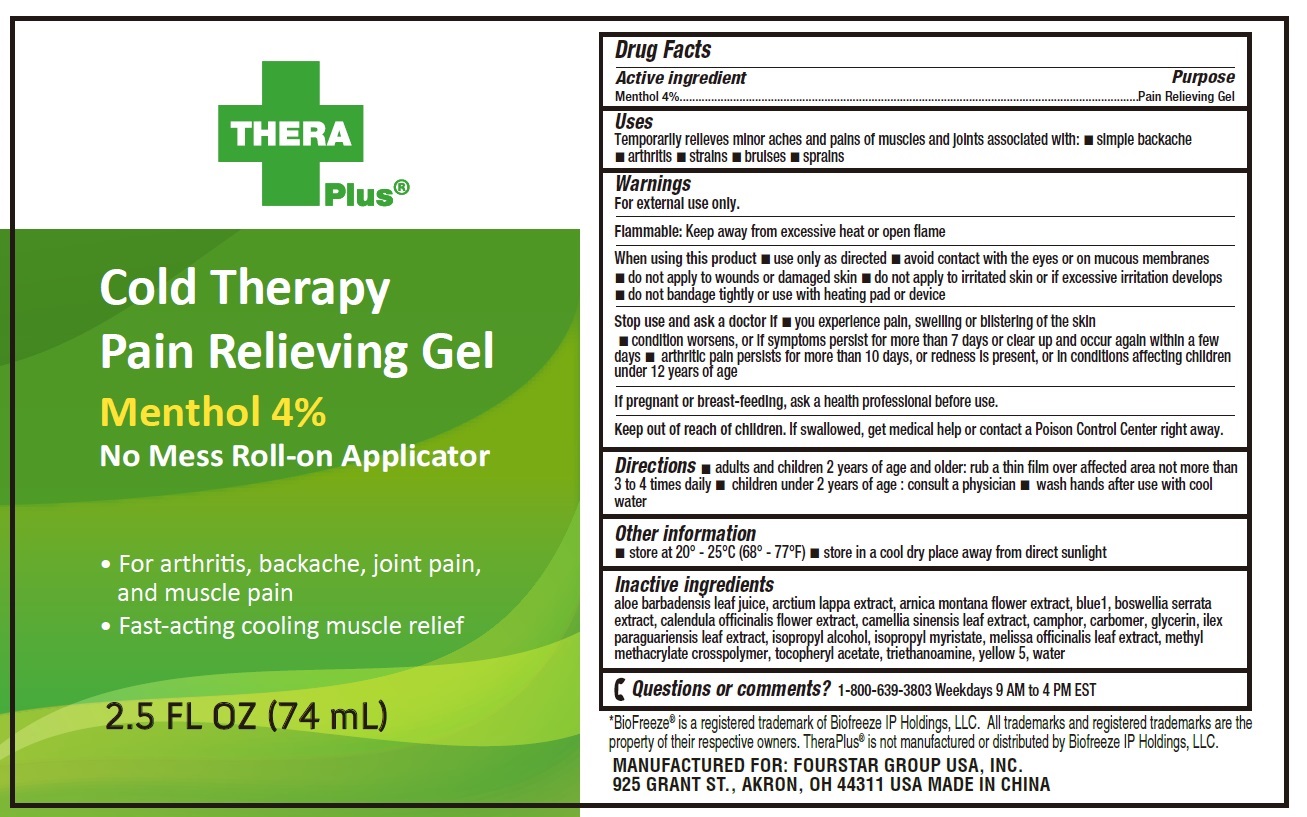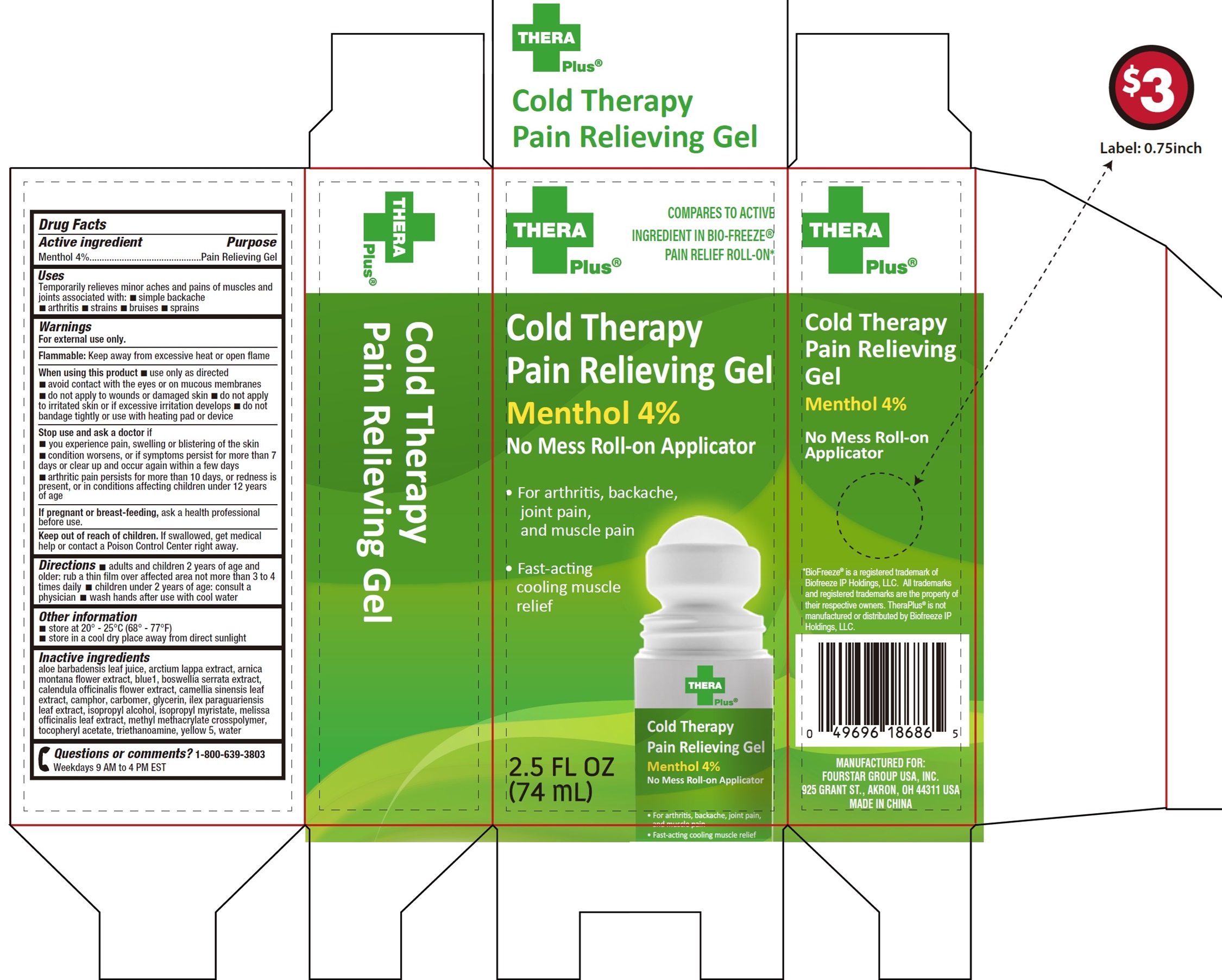 DRUG LABEL: Thera Plus Cold Therapy Pain Relieving Menthol
NDC: 80684-101 | Form: GEL
Manufacturer: Fourstar Group USA, Inc.
Category: otc | Type: HUMAN OTC DRUG LABEL
Date: 20231127

ACTIVE INGREDIENTS: MENTHOL 40 mg/1 mL
INACTIVE INGREDIENTS: ALOE VERA LEAF; ARNICA MONTANA FLOWER; FD&C BLUE NO. 1; INDIAN FRANKINCENSE; CALENDULA OFFICINALIS FLOWER; GREEN TEA LEAF; CARBOMER HOMOPOLYMER, UNSPECIFIED TYPE; GLYCERIN; ILEX PARAGUARIENSIS LEAF; ISOPROPYL ALCOHOL; ISOPROPYL MYRISTATE; MELISSA OFFICINALIS LEAF; .ALPHA.-TOCOPHEROL ACETATE; TROLAMINE; FD&C YELLOW NO. 5; WATER

Thera Plus Cold Therapy Pain Relieving Gel Menthol

Active ingredient

Menthol 4%

Purpose

Pain Relieving Gel

Uses

Temporarily relieves minor aches and pains of muscles and joints associated with: • simple backache • arthritis • strains • bruises • sprains

Warnings

For external use only.

Flammable:Keep away from excessive heat or open flame

When using this product

- use only as directed
- avoid contact with the eyes or on mucous membranes
- do not apply to wounds or damaged skin
- do not apply to irritated skin or if excessive irritation develops
- do not bandage tightly or use with heating pad or device

Stop use and ask a doctor if

- you experience pain, swelling or blistering of the skin
- condition worsens, or if symptoms persist for more than 7 days or clear up and occur again within a few days
- arthritic pain persists for more than 10 days, or redness is present, or in conditions affecting children under 12 years of age

If pregnant or breast-feeding,

ask a health professional before use.

Keep out of reach of children.

If swallowed, get medical help or contact a Poison Control Center right away.

Directions

- adults and children 2 years of age and older; rub a thin film over affected area not more than 3 to 4 times daily
- children under 2 years of age: consult a physician
- wash hands after use with cool water

Other information

- store at 20° - 25°C (68° - 77°F)
- store in a cool dry place away from direct sunlight

Inactive ingredients

aloe barbadensis leaf juice, arctium lappa extract, arnica montana flower extract, blue1, boswellia serrata extract, calendula officinalis flower extract, camellia sinensis leaf extract, camphor, carbomer, glycerin, ilex paraguariensis leaf extract, isopropyl alcohol, isopropyl myristate, melissa officinalis leaf extract, methyl methacrylate crosspolymer, tocopheryl acetate, triethanoamine, yellow 5, water

Questions or comments?

1-800-639-3803 Weekdays 9 AM to 4 PM EST